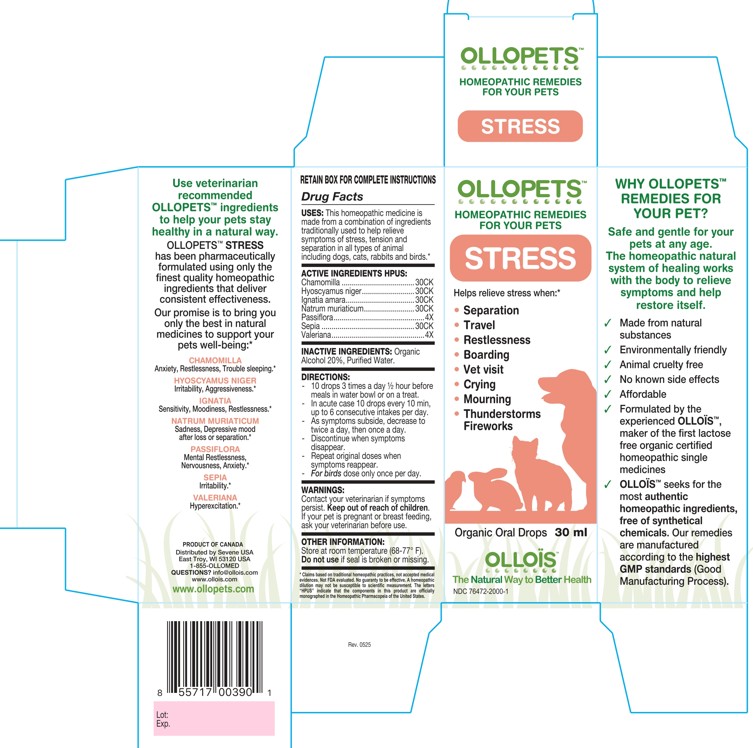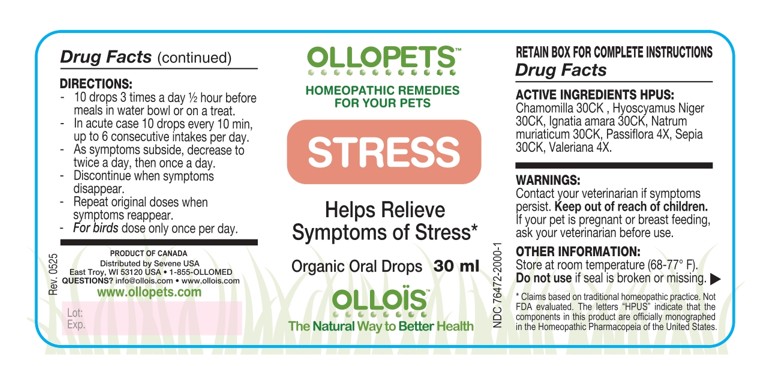 DRUG LABEL: OLLOPETS STRESS
NDC: 76472-2000 | Form: SOLUTION
Manufacturer: SEVENE USA
Category: homeopathic | Type: OTC ANIMAL DRUG LABEL
Date: 20260217

ACTIVE INGREDIENTS: MATRICARIA CHAMOMILLA 30 [hp_C]/100 mL; HYOSCYAMUS NIGER 30 [hp_C]/100 mL; STRYCHNOS IGNATII SEED 30 [hp_C]/100 mL; SODIUM CHLORIDE 30 [hp_C]/100 mL; PASSIFLORA EDULIS WHOLE 4 [hp_X]/100 mL; SEPIA OFFICINALIS JUICE 30 [hp_C]/100 mL; VALERIAN 4 [hp_X]/100 mL
INACTIVE INGREDIENTS: ALCOHOL; WATER

SEVENE USA - OLLOPETS - STRESS

ACTIVE INGREDIENT HPUS

Chamomilla ....................................30CK
Hyoscyamus niger..........................30CK
Ignatia amara..................................30CK
Natrum muriaticum.........................30CK
Passiflora.............................................4X
Sepia ..............................................30CK
Valeriana..............................................4X